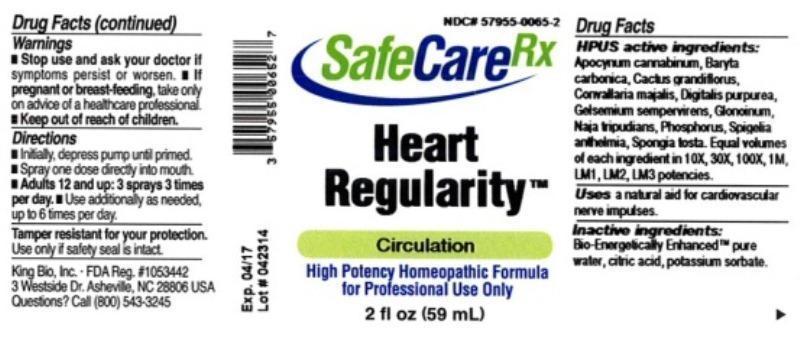 DRUG LABEL: Heart Regularity
NDC: 57955-0065 | Form: LIQUID
Manufacturer: King Bio Inc.
Category: homeopathic | Type: HUMAN OTC DRUG LABEL
Date: 20140515

ACTIVE INGREDIENTS: APOCYNUM CANNABINUM ROOT 10 [hp_X]/59 mL; BARIUM CARBONATE 10 [hp_X]/59 mL; SELENICEREUS GRANDIFLORUS STEM 10 [hp_X]/59 mL; CONVALLARIA MAJALIS 10 [hp_X]/59 mL; DIGITALIS 10 [hp_X]/59 mL; GELSEMIUM SEMPERVIRENS ROOT 10 [hp_X]/59 mL; NITROGLYCERIN 10 [hp_X]/59 mL; NAJA NAJA VENOM 10 [hp_X]/59 mL; PHOSPHORUS 10 [hp_X]/59 mL; SPIGELIA ANTHELMIA 10 [hp_X]/59 mL; SPONGIA OFFICINALIS SKELETON, ROASTED 10 [hp_X]/59 mL
INACTIVE INGREDIENTS: WATER; CITRIC ACID MONOHYDRATE; POTASSIUM SORBATE

Heart Regularity™

ACTIVE INGREDIENT

Drug Facts__________________________________________________________________________________________________________

HPUS activeingredients: Apocynum cannabinum, Baryta carbonica, Cactus grandiflorus, Convallaria majalis, Digitalis purpurea, Gelsemium sempervirens, Glonoinum, Naja tripudians, Phosphorus, Spigelia anthelmia, Spongia tosta. Equal volumes of each ingredient in 10X, 30X, 100X, 1M, LM1, LM2, LM3 potencies.

INDICATIONS AND USAGE

Uses a natural aid for cardiovascular nerve impulses.

Inactive Ingredients:

Bio-Energetically Enhanced™ pure water, citric acid and potassium sorbate.

Warnings

- Stop use and ask your doctor if symptoms persist or worsen.
- If pregnant or breast-feeding, take only on advice of a healthcare professional.

- Keep out of reach of children.

Directions

- Initially, depress pump until primed.
- Spray one dose directly into mouth.
- Adults 12 and up: 3 sprays 3 times per day.
- Use additionally as needed, up to 6 times per day.

OTHER SAFETY INFORMATION

Tamper resistant for your protection. Use only if safety seal is intact.

PURPOSE

Uses a natural aid for cardiovascular nerve impulses.